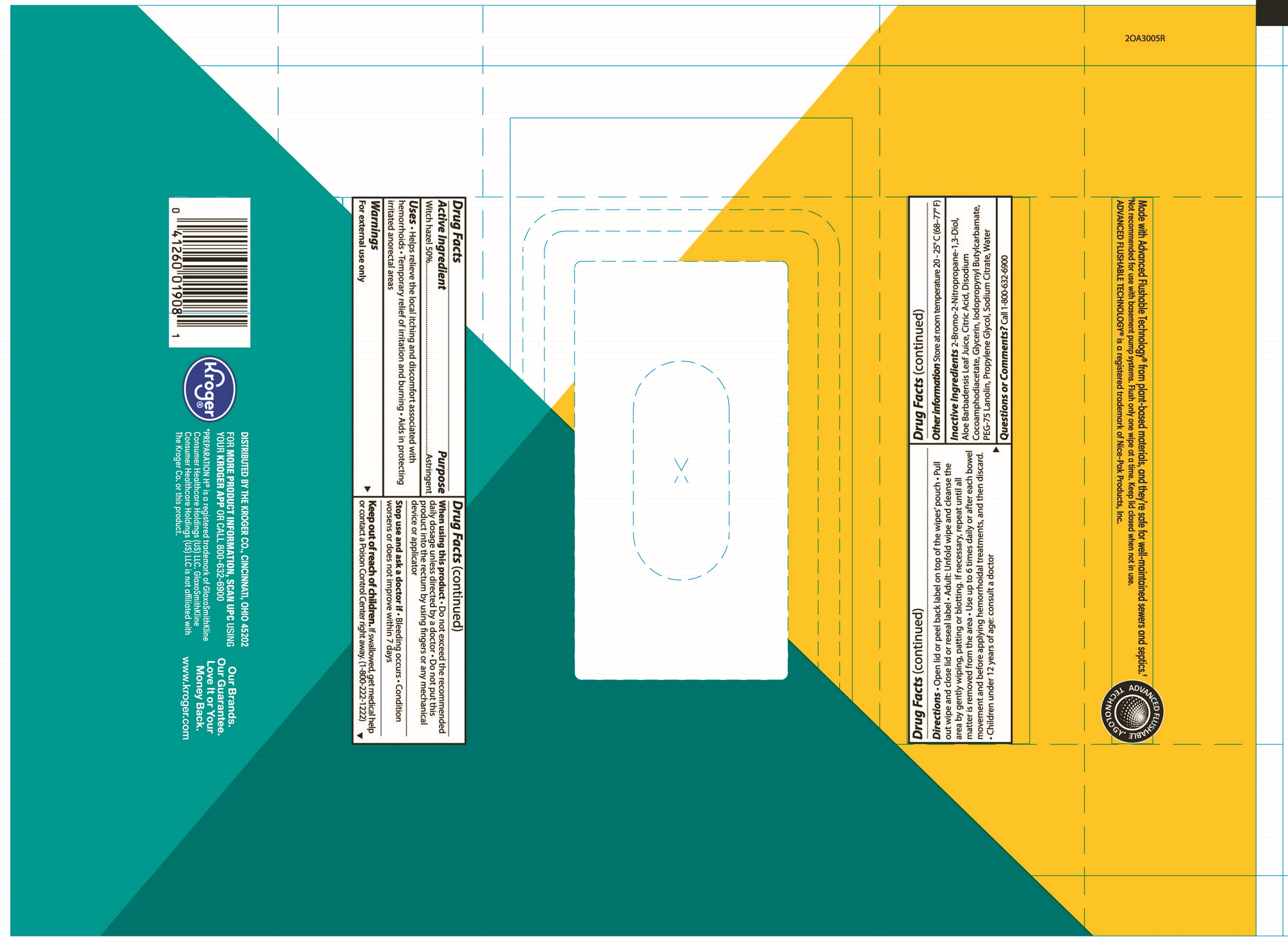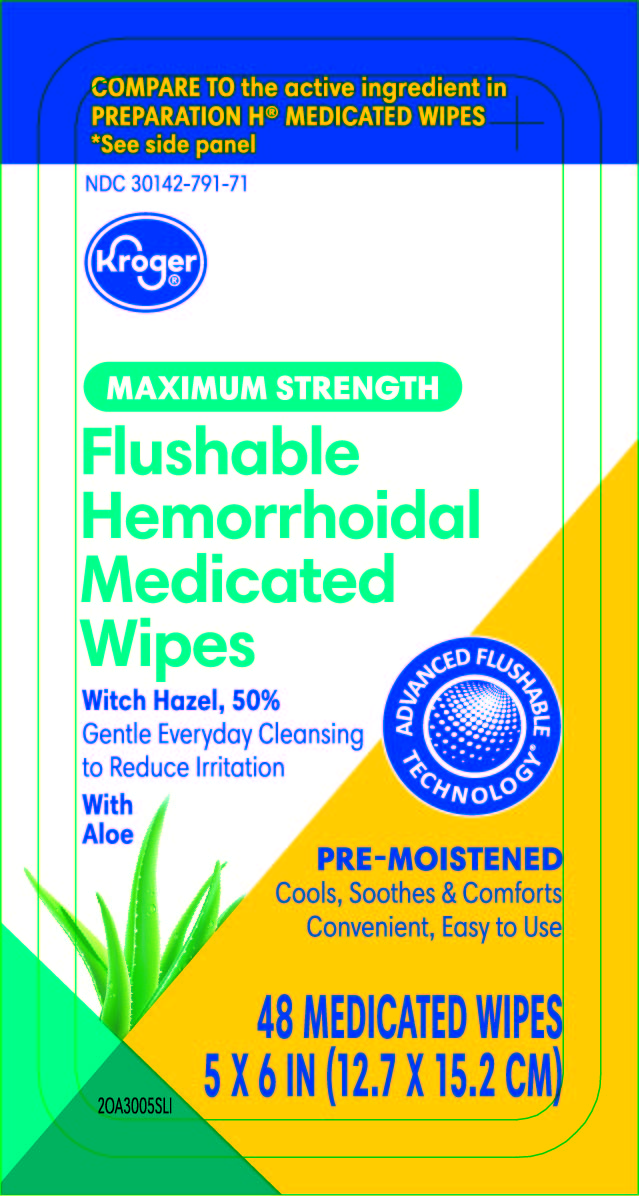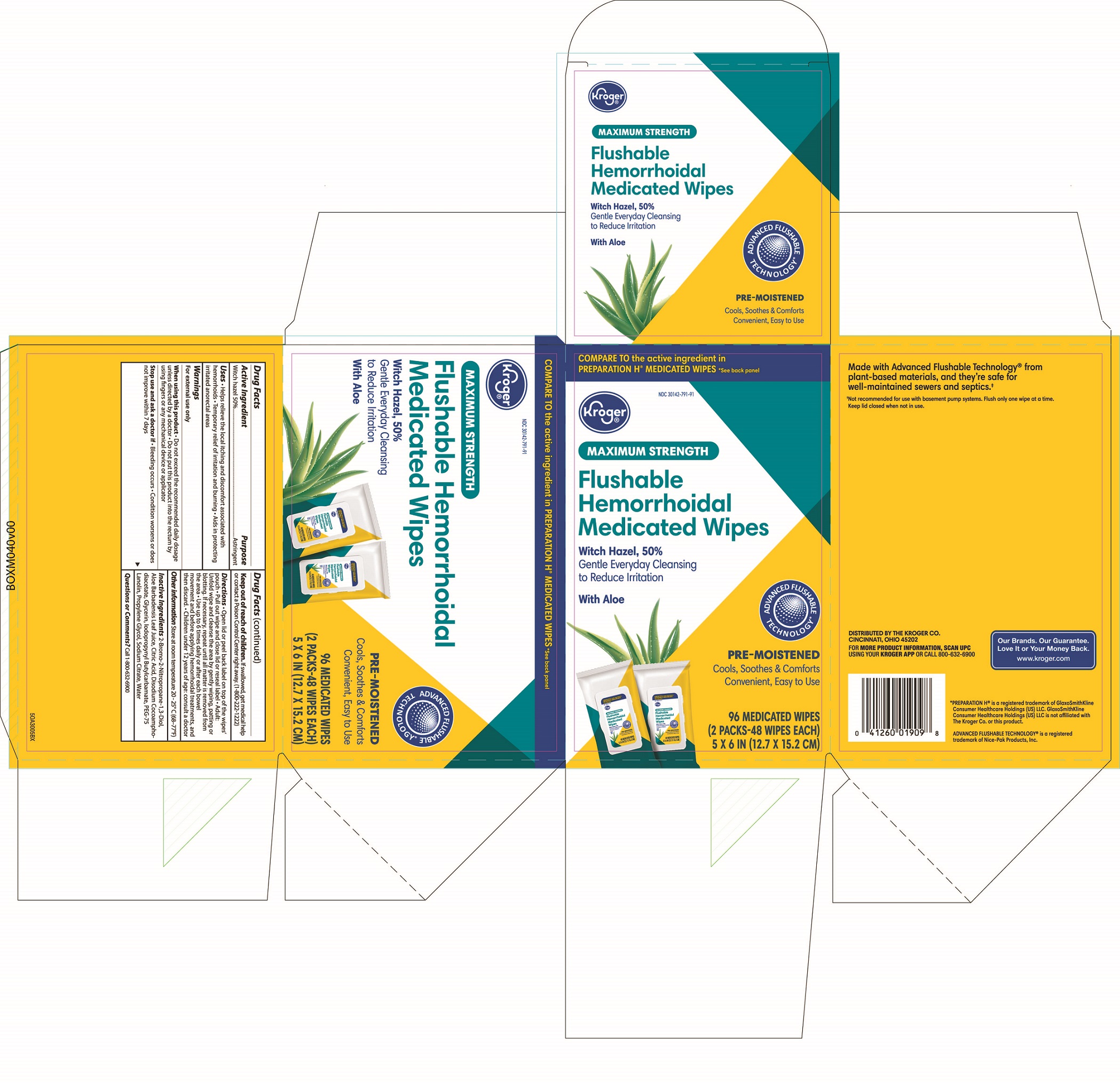 DRUG LABEL: KROGER MEDICATED WIPES
NDC: 30142-791 | Form: SWAB
Manufacturer: The Kroger Co.
Category: otc | Type: HUMAN OTC DRUG LABEL
Date: 20241107

ACTIVE INGREDIENTS: WITCH HAZEL 0.5 g/1 g
INACTIVE INGREDIENTS: WATER; SODIUM CITRATE; BRONOPOL; GLYCERIN; PROPYLENE GLYCOL; IODOPROPYNYL BUTYLCARBAMATE; DISODIUM COCOAMPHODIACETATE; ALOE VERA LEAF; PEG-75 LANOLIN; CITRIC ACID MONOHYDRATE

Kroger medicated wipes, NDC number 30142-791

Active ingredient

Witch hazel 50%

Purpose

Astringent

Uses

- helps relieve the local itching and disconfort associated with hemorrhoids
- temporary relief of irritation and burning
- aids in protecting irritated anorectal areas

Warnings

For external use only

When using this product

- do not exceed the recommended daily dosage unless directed by a doctor
- do not put this product into the rectum by using fingers or any mechanical device or applicator

Stop use and ask doctor if

- bleeding occurs
- conditions worsens or does not improve within 7 days

Keep out of reach of children

If swallowed, get medical help or contact a Poison Control Center right away. (1-800-222-1222)

Directions

- adult: unfold wipe and cleanse the area by gently wiping, patting or blotting. If necessary, repeat until all matter is removed from the area.
- use up to 6 times daily or after each bowel movement and before applying topical hemorrhoidal treatments, and then discard
- children under 12 years of age: consult a doctor

Other information

- store at room temperature 20-25ºC (68 - 77ºF)
- for vaginal care - cleanse the area by gently wiping, pating or blotting. Repeat as needed.
- for use as a moist compress - if necessary, first cleanse the area as previously described. Fold wipe to desired size and place in contact with tissue for a soothing and cooling effect. Leave in place for up to 15 minutes and repeat as needed.

Inactive ingredients

2-Bromo-2-Nitropropane-1,3-Diol, Aloe Barbadensis Leaf Juice, Citric Acid, Disodium Cocoamphodiacetate, Glycerin, Iodopropynyl Butylcarbamate, PEG-75 Lanolin, Propylene Glycol, Sodium Citrate, Water